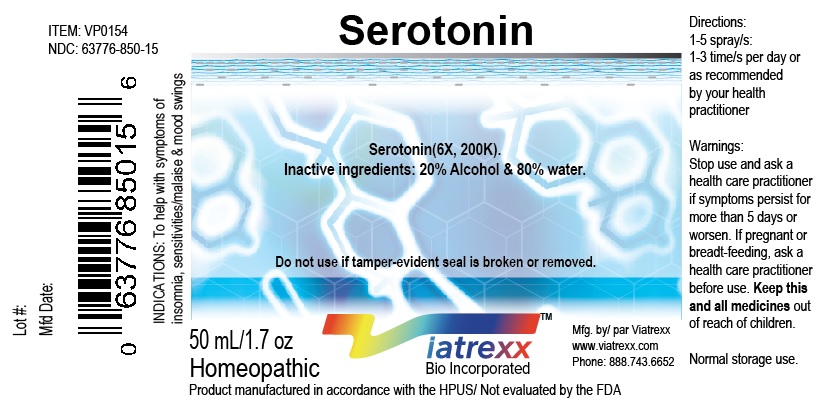 DRUG LABEL: Serotonin
NDC: 63776-850 | Form: SPRAY
Manufacturer: VIATREXX BIO INCORPORATED
Category: homeopathic | Type: HUMAN OTC DRUG LABEL
Date: 20180111

ACTIVE INGREDIENTS: Serotonin Hydrochloride 200 [kp_C]/1 mL
INACTIVE INGREDIENTS: Alcohol; Water

Serotonin

Active Ingredients

Serotonin (6X, 200K).

Purpose:

Serotonin | Neurological support

Description

Viatrexx- Serotonin is a homeopathic product composed of physiological (low dose and low low dose) natural micro nutrients. These nano particles are designed to nourish the system.

Uses

To help with the support of health aging & vigor.

Warnings

Stop use and ask a health care practitioner if symptoms persist for more than five days or worsen. If pregnant or breastfeeding, ask a health care practitioner before use.

Dosage

1-3 spray(s); 1-3 time(s) per day or as recommended by your health care practitioner.

KEEP OUT OF REACH OF CHILDREN

Keep this and all medicines out of reach of children.

Product Availability

Product may be acquired in 0.5, 30 ,50, 100, 250 mL bottles.

Inactive Ingredients

20% Alcohol and 80% Water

Other Information

Normal storage use.
Do not use if tamper-evident seal is broken or removed.

References Upon Request

To report SUSPECTED ADVERSE REACTIONS, contact the FDA at 1-800-FDA-1088 or www.fda.gov/medwatch
Distributed by Viatrexx Bio Incorporated
Newark, DE, USA, 19713
Manufactured by
8046255 Canada Inc
Beloeil, Qc, J3G 6S3
Date of last revision March 2019
For questions and comments
Info@Viatrexx.com
www.Viatrexx.com

PACKAGE LABEL.PRINCIPAL DISPLAY PANEL

NDC: 63776-850-11
Item: VP0154
Viatrexx Bio Incorporated
Viatrexx- Serotonin
Box of 1 X 0.5 mL ampule
For Oral and Topical Use
Expiry date: Lot #:
Manufactured for:
Viatrexx Bio Incorporated Newark, DE, USA, 19713
www.Viatrexx.com
Ingredients, homeopathic
See insert or www.viatrexx.com
Inactives: Alcohol 20%, Water 80%

NDC: 63776-850-14
Item: VP0154
Viatrexx Bio Incorporated
Viatrexx- Serotonin
Box of 1 X 30 mL spray bottle
For Oral and Topical Use
Expiry date: Lot #:
Manufactured for:
Viatrexx Bio Incorporated Newark, DE, USA, 19713
www.Viatrexx.com
Ingredients, homeopathic
See insert or www.viatrexx.com
Inactives: Alcohol 20%, Water 80%

NDC: 63776-850-15
Item: VP0154
Viatrexx Bio Incorporated
Viatrexx- Serotonin
Box of 1 X 50 mL spray bottle
For Oral and Topical Use
Expiry date: Lot #:
Manufactured for:
Viatrexx Bio Incorporated Newark, DE, USA, 19713
www.Viatrexx.com
Ingredients, homeopathic
See insert or www.viatrexx.com
Inactives: Alcohol 20%, Water 80%

NDC: 63776-850-16
Item: VP0154
Viatrexx Bio Incorporated
Viatrexx- Serotonin
Box of 1 X 100 mL bottle
For Oral and Topical Use
Expiry date: Lot #:
Manufactured for:
Viatrexx Bio Incorporated Newark, DE, USA, 19713
www.Viatrexx.com
Ingredients, homeopathic
See insert or www.viatrexx.com
Inactives: Alcohol 20%, Water 80%

NDC: 63776-850-17
Item: VP0154
Viatrexx Bio Incorporated
Viatrexx- Serotonin
Box of 1 X 250 mL bottle
For Oral and Topical Use
Expiry date: Lot #:
Manufactured for:
Viatrexx Bio Incorporated Newark, DE, USA, 19713
www.Viatrexx.com
Ingredients, homeopathic
See insert or www.viatrexx.com
Inactives: Alcohol 20%, Water 80%